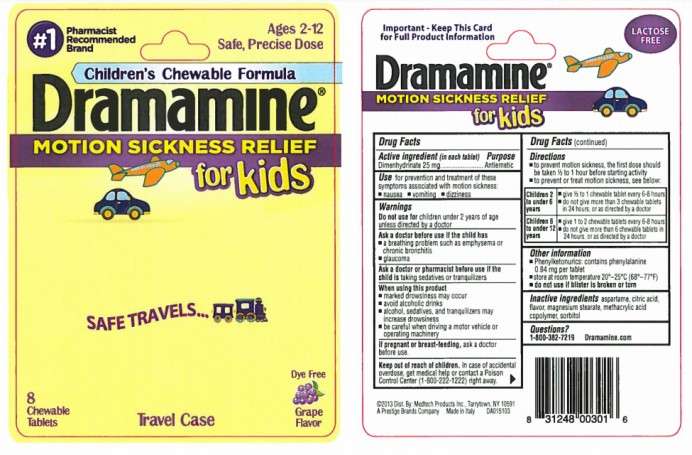 DRUG LABEL: Dramamine for Kids
NDC: 63029-910 | Form: TABLET, CHEWABLE
Manufacturer: Medtech Products Inc.
Category: otc | Type: HUMAN OTC DRUG LABEL
Date: 20250506

ACTIVE INGREDIENTS: DIMENHYDRINATE 25 mg/1 1
INACTIVE INGREDIENTS: ASPARTAME; ANHYDROUS CITRIC ACID; GRAPE; MAGNESIUM STEARATE; METHACRYLIC ACID - METHYL METHACRYLATE COPOLYMER (1:1); SORBITOL

Dramamine Tablets Chewable for Kids

Drug Facts

Active Ingredient

(in each tablet)

Dimenhydrinate 25 mg

Purpose

Antiemetic

Use

for prevention and treatment of these symptoms associated with motion sickness:

nausea dizziness vomiting

Warnings

Do not use for

children under 2 years of age unless directed by a doctor

Ask a doctor before use if the child has

- A breathing problem such as emphysema or chronic bronchitis
- Glaucoma

Ask a doctor before use if the child is

taking sedatives or tranquilizers

When using this product

- Marked drowsiness may occur
- Avoid alcoholic drinks
- Alcohol, sedatives, and tranquilizers may increase drowsiness
- Be careful when dricing a motor vehicle or opereating machinery

If pregnant or breast-feeding,

ask a doctor before use

Keep out of reach of children.

In case of accidental overdose, get medical help or contact a Poison Contorl Center (1-800-222-1222) right away.

Directions

- To prevent motion sickness, the first dose should be taken ½ to 1 hour before starting activity
- To prevent or treat motion sickness see below:

Children 2 to under 6 years

- Give ½ to 1 chewable tablet every 6-8 hours
- Do not give more than 3 chewable tablets in 24 hours or as directed by a doctor

Children 6 to 12 years

- Give 1 to 2 chewable talets every 6-8 hours
- Do not give more than 6 chewable tablets in 24 hours, or as directed by a doctor

Other information

- Phenylketonurics: contains phenylalanine 0.38 mg per tablet
- Store at room temperature 20◦-25◦C (68◦-77◦F)
- Do not use if blister is broken or torn

Inactive ingredients

aspartame, citric acid, flavors, magnesium stearate, methacrylic acid copolymer, sorbitol

Questions?

1-800-382-7219 Dramamine.com

Principal display panel

Children’s Chewable Formula

Dramamine®

8 Chewable Tablets
Travel case